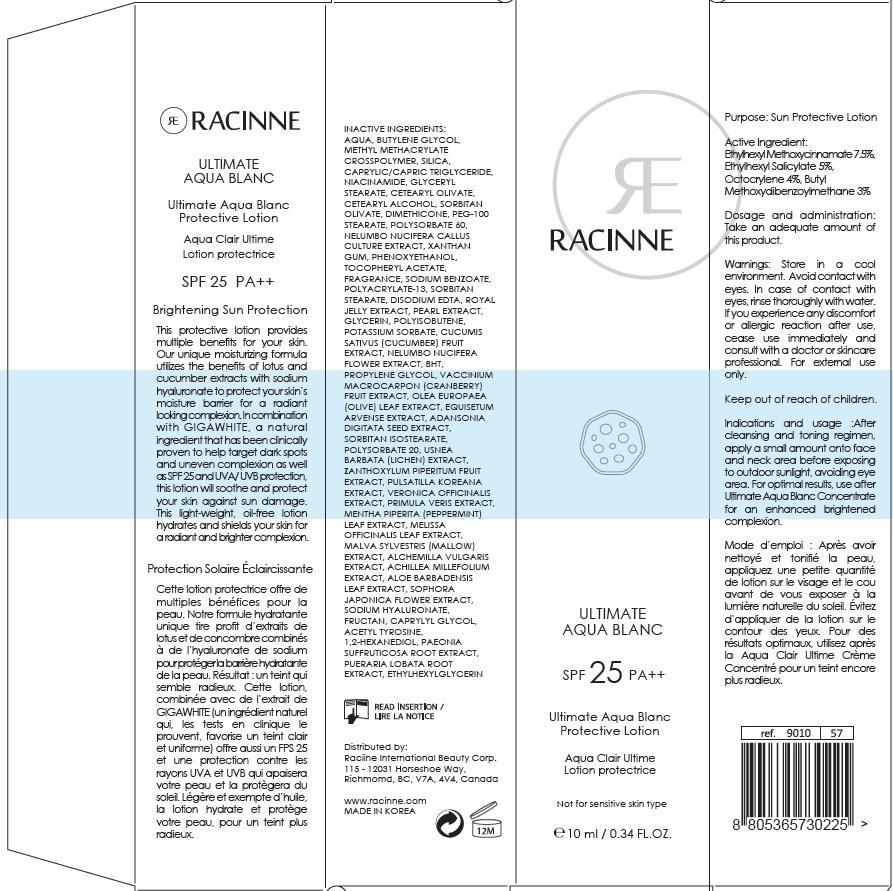 DRUG LABEL: ULTIMATE AQUA BLANC PROTECTIVE
NDC: 69015-110 | Form: LOTION
Manufacturer: Racinne (Hong Kong) Limited
Category: otc | Type: HUMAN OTC DRUG LABEL
Date: 20140625

ACTIVE INGREDIENTS: OCTINOXATE 0.75 mg/10 mL; OCTISALATE 0.5 mg/10 mL; OCTOCRYLENE 0.4 mg/10 mL; AVOBENZONE 0.3 mg/10 mL
INACTIVE INGREDIENTS: WATER; BUTYLENE GLYCOL

ACTIVE INGREDIENT

Active Ingredient: Ethylhexyl Methoxycinnamate 7.5%, Ethylhexyl Salicylate 5%, Octocrylene 4%, Butyl Methoxydibenzoylmethane 3%

INACTIVE INGREDIENT

Inactive ingredients:
AQUA, BUTYLENE GLYCOL, METHYL METHACRYLATE CROSSPOLYMER, SILICA, CAPRYLIC/ CAPRIC TRIGLYCERIDE, NIACINAMIDE, GLYCERYL STEARATE, CETEARYL OLIVATE, CETEARYL ALCOHOL, SORBITAN OLIVATE, DIMETHICONE, PEG-100 STEARATE, POLY-SORBATE 60, NELUMBO NUCIFERA CALLUS CULTURE EXTRACT, XANTHAN GUM, PHENOXYETHANOL, TOCOPHERYL ACETATE, FRAGRANCE, SODIUM BENZOATE, POLYACRYLATE-13, SORBITAN STEARATE, DISODIUM EDTA, ROYAL JELLY EXTRACT, PEARL EXTRACT, GLYCERIN, POLYISOBUTENE, POTASSIUM SORBATE, CUCUMIS SATIVUS (CUCUMBER) FRUIT EXTRACT, NELUMBO NUCIFERA FLOWER EXTRACT, BHT, PROPYLENE GLYCOL, VACCINIUM MACROCARPON (CRANBERRY) FRUIT EXTRACT, OLEA EUROPAEA (OLIVE) LEAF EXTRACT, EQUISETUM ARVENSE EXTRACT, ADANSONIA DIGITATA SEED EXTRACT, SORBITAN ISOSTEARATE, POLYSORBATE 20, USNEA BARBATA (LICHEN) EXTRACT, ZANTHOXYLUM PIPERITUM FRUIT EXTRACT, PULSATILLA KOREANA EXTRACT, VERONICA OFFICINALIS EXTRACT, PRIMULA VERIS EXTRACT, MENTHA PIPERITA (PEPPERMINT) LEAF EXTRACT, MELISSA OFFICINALIS LEAF EXTRACT, MALVA SYLVESTRIS (MALLOW) EXTRACT, ALCHEMILLA VULGARIS EXTRACT, ACHILLEA MILLEFOLIUM EXTRACT, ALOE BARBADENSIS LEAF EXTRACT, SOPHORA JAPONICA FLOWER EXTRACT, SODIUM HYALURONATE, FRUCTAN, CAPRYLYL GLYCOL, ACETYL TYROSINE, 1,2- HEXANEDIOL, PAEONIA SUFFRUTICOSA ROOT EXTRACT, PUERARIA LOBATA ROOT EXTRACT, ETHYLHEXYLGLYCERIN

PURPOSE

Purpose: Sun Protective Lotion

WARNINGS

Store in a cool environment.
Avoid contact with eyes.
In case of contact with eyes, rinse thoroughly with water.
If you experience any discomfort or allergic reaction after use, cease use immediately and consult with a doctor or skincare professional.
For external use only.

KEEP OUT OF REACH OF CHILDREN

INDICATIONS AND USAGE

After cleansing and toning regimen, apply a small amount onto face and neck area before exposing to outdoor sunlight, avoiding eye area.
For optimal results, use after Ultimate Aqua Blanc Concentrate for an enhanced brightened complexion.

Dosage and administration: Take an adequate amount of this product.